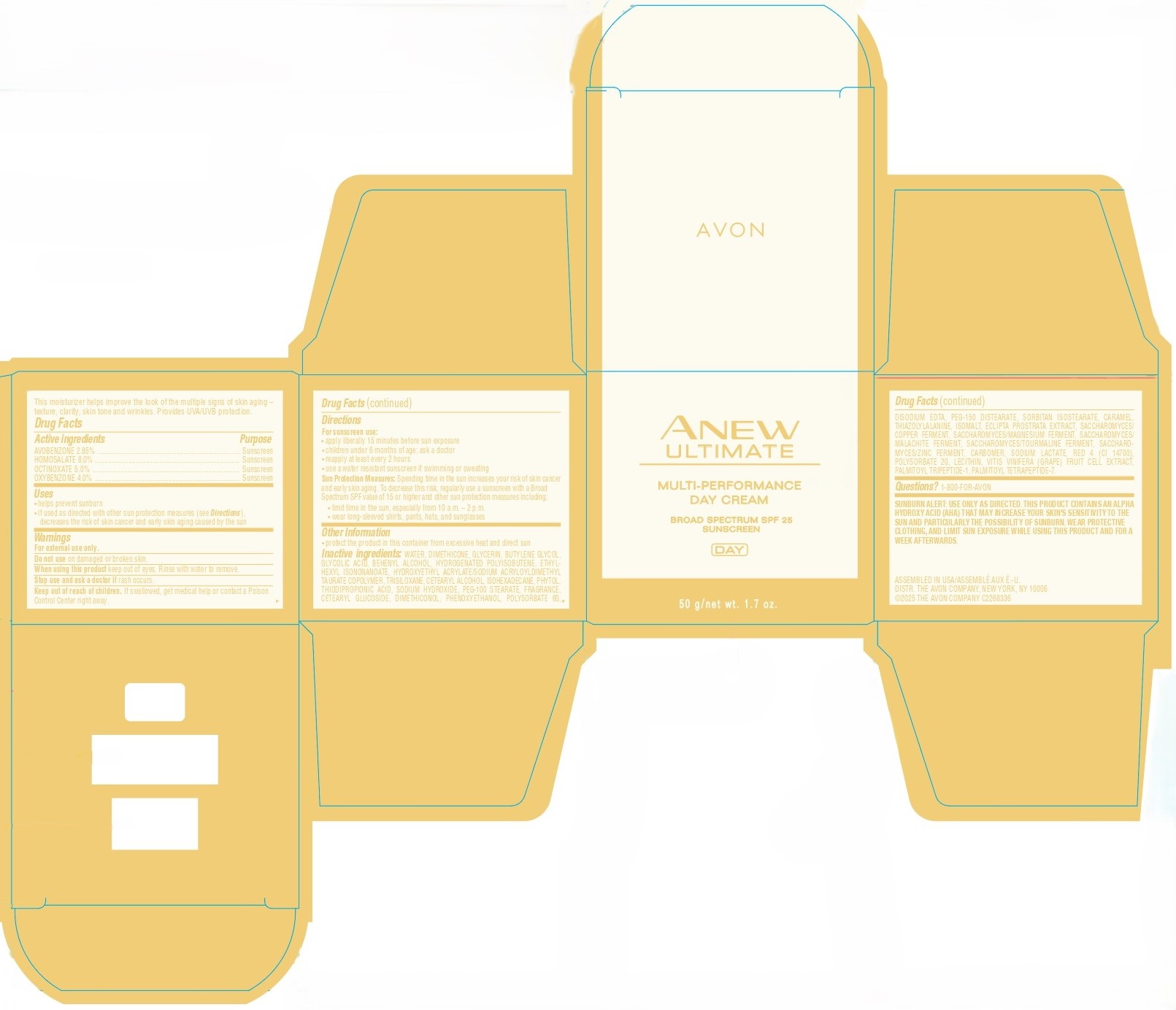 DRUG LABEL: AVON ANEW ULTIMATE MULTI-PERFORMANCE DAY BROAD SPECTRUM SPF 25 SUNSCREEN
NDC: 10096-2651 | Form: CREAM
Manufacturer: The Avon Company
Category: otc | Type: HUMAN OTC DRUG LABEL
Date: 20260128

ACTIVE INGREDIENTS: OCTINOXATE 50 mg/1 g; HOMOSALATE 80 mg/1 g; OXYBENZONE 40 mg/1 g; AVOBENZONE 28.5 mg/1 g
INACTIVE INGREDIENTS: ETHYLHEXYL ISONONANOATE; THIODIPROPIONIC ACID; CETEARYL GLUCOSIDE; SODIUM LACTATE; WATER; PHENOXYETHANOL; ISOMALT; RED 4; BEHENYL ALCOHOL; HYDROGENATED POLYISOBUTENE (450 MW); CARBOMER; PALMITOYL TRIPEPTIDE-1; BUTYLENE GLYCOL; PEG-100 STEARATE; DIMETHICONE; GLYCOLIC ACID; PHYTOL, (E)-; DIMETHICONOL (40 CST); SORBITAN ISOSTEARATE; GLYCERIN; TRISILOXANE; CETEARYL ALCOHOL; ECLIPTA PROSTRATA LEAF; CARAMEL; PALMITOYL TETRAPEPTIDE-7; POLYSORBATE 20; ISOHEXADECANE; EDETATE DISODIUM; THIAZOLYLALANINE; HYDROXYETHYL ACRYLATE/SODIUM ACRYLOYLDIMETHYL TAURATE COPOLYMER (45000 MPA.S AT 1%); SODIUM HYDROXIDE; POLYSORBATE 60; PEG-150 DISTEARATE

1186048AM_Anew Ultimate Day Multi Perform SPF 25 (Listing due to reform)

Drug Facts

AVOBENZONE 2.85%
HOMOSALATE 8.0%
OCTINOXATE 5.0%
OXYBENZONE 4.0%

Purpose

Sunscreen

Uses

- helps prevent sunburn
- if used as directed with other sun protection measures (see Directions), decrease the rist of skin cancer and early skin aging caused by the sun

Warnings

For external use only.

Do not use on damaged or broken skin.

When using this product keep out of eyes. Rinse with water to remove.

Stop use and ask a doctor if rash occurs.

Keep out of reach of children. If swallowed, get medical help or contact a Poison Control Center right away.

Directions

For sunscreen use:

- apply liberally 15 minutes before sun exposure
- children under 6 months of age: ask a doctor
- reapply at least every 2 hours
- use a water resistant sunscreen if swimming or sweating

Sun Protection Measures: Spending time in the sun increases your risk of skin cancer and early skin aging. To decrease this risk, regularly use a sunscreen with a Broad Spectrum SPF value of 15 or higher and other sun protection measures including:

- limit time in the sun, especially from 10 a.m. – 2 p.m.
- wear long-sleeved shirts, pants, hats, and sunglasses

Other Information

• protect the product in this container from excessive heat and direct sun

Inactive Ingredients:

WATER, DIMETHICONE, GLYCERIN, BUTYLENE GLYCOL, GLYCOLIC ACID, BEHENYL ALCOHOL, HYDROGENATED POLYISOBUTENE, ETHYLHEXYL ISONONANOATE, HYDROXYETHYL ACRYLATE/SODIUM ACRYLOYLDIMETHYL TAURATE COPOLYMER, TRISILOXANE, CETEARYL ALCOHOL, ISOHEXADECANE, PHYTOL, THIODIPROPIONIC ACID, SODIUM HYDROXIDE, PEG-100 STEARATE, FRAGRANCE, CETEARYL GLUCOSIDE, DIMETHICONOL, PHENOXYETHANOL, POLYSORBATE 60, DISODIUM EDTA, PEG-150 DISTEARATE, SORBITAN ISOSTEARATE, CARAMEL, THIAZOLYLALANINE, ISOMALT, ECLIPTA PROSTRATA EXTRACT, SACCHAROMYCES/COPPER FERMENT, SACCHAROMYCES/MAGNESIUM FERMENT, SACCHAROMYCES/MALACHITE FERMENT, SACCHAROMYCES/TOURMALINE FERMENT, SACCHAROMYCES/ZINC FERMENT, CARBOMER, SODIUM LACTATE, RED 4 (CI 14700), POLYSORBATE 20, LECITHIN, VITIS VINIFERA (GRAPE) FRUIT CELL EXTRACT, PALMITOYL TRIPEPTIDE-1, PALMITOYL TETRAPEPTIDE-7.

Questions?

1-800-FOR-AVON

Principal Display Panel:

AVON
ANEW
ULTIMATE
MULTI-PERFORMANCE
DAY CREAM
BROAD SPECTRUM SPF 25
SUNSCREEN
DAY
50 g / net wt. 1.7 oz.
This moisturizer helps improve the look of the multiple signs of skin aging -
texture, clarity, skin tone and wrinkles. Provides UVA/UVB protection.
To order, contact your Avon Independent Sales Representative or call:
1-800-FOR-AVON www.avon.com
ASSEMBLED IN USA/ASSEMBLE AUX E.-U.
DISTR. THE AVON COMPANY, NEW YORK, NY 10006
©2025 THE AVON COMPANY C2268336